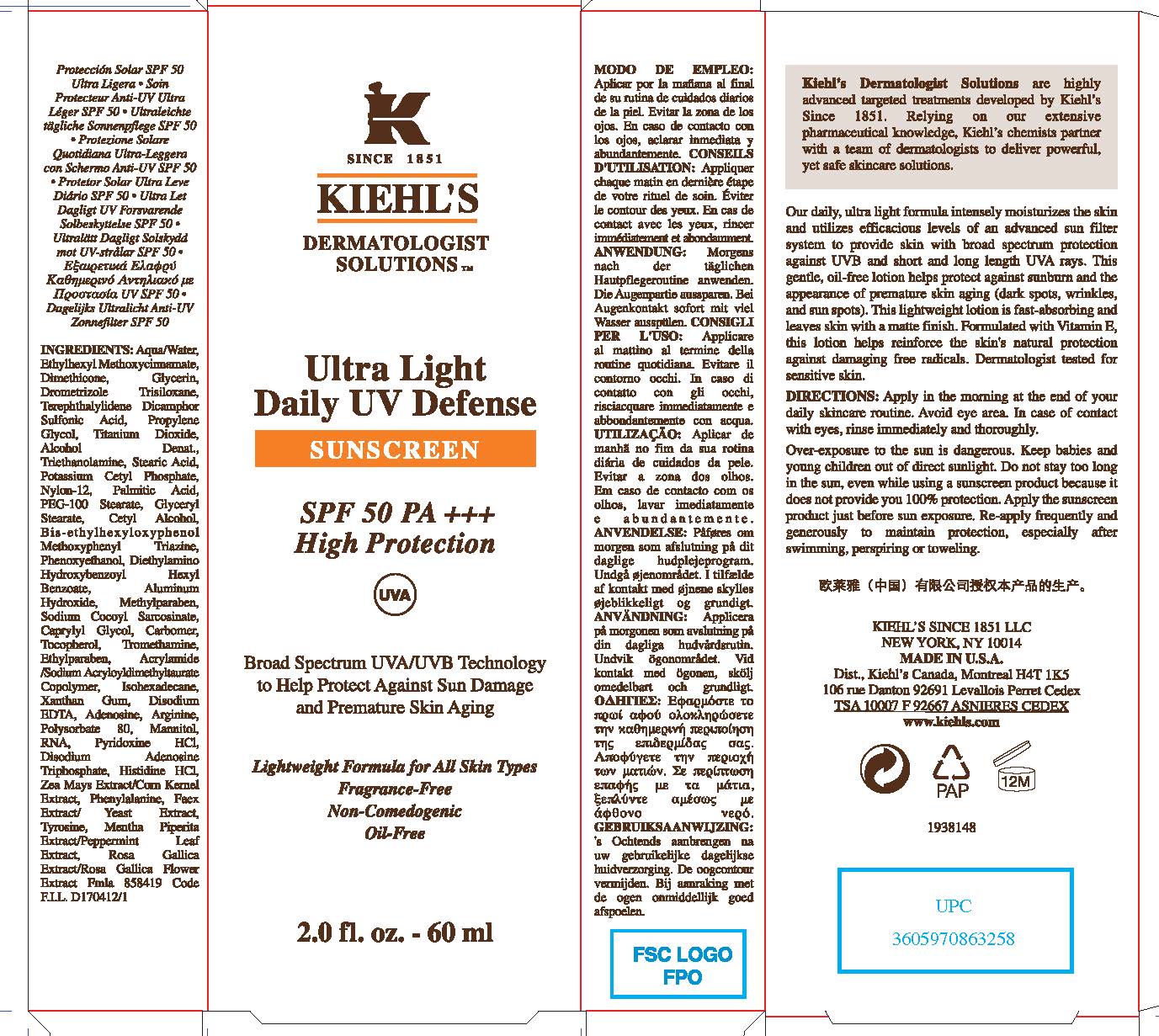 DRUG LABEL: Kiehls Ultra Light Daily UV Defense Sunscreen
NDC: 49967-258 | Form: LOTION
Manufacturer: L'Oreal USA Products Inc.
Category: otc | Type: HUMAN OTC DRUG LABEL
Date: 20260107

ACTIVE INGREDIENTS: DROMETRIZOLE TRISILOXANE 40 mg/1 mL; OCTINOXATE 67.5 mg/1 mL; ECAMSULE 120 mg/1 mL
INACTIVE INGREDIENTS: WATER; DIMETHICONE; GLYCERIN; PROPYLENE GLYCOL; TITANIUM DIOXIDE; ALCOHOL; TROLAMINE; STEARIC ACID; POTASSIUM CETYL PHOSPHATE; NYLON-12; PALMITIC ACID; PEG-100 STEARATE; GLYCERYL MONOSTEARATE; CETYL ALCOHOL; BEMOTRIZINOL; PHENOXYETHANOL; DIETHYLAMINO HYDROXYBENZOYL HEXYL BENZOATE; ALUMINUM HYDROXIDE; METHYLPARABEN; SODIUM COCOYL SARCOSINATE; CAPRYLYL GLYCOL; CARBOMER HOMOPOLYMER, UNSPECIFIED TYPE; TOCOPHEROL; TROMETHAMINE; ETHYLPARABEN; ISOHEXADECANE; XANTHAN GUM; EDETATE DISODIUM ANHYDROUS; ADENOSINE; ARGININE; POLYSORBATE 80; MANNITOL; PYRIDOXINE HYDROCHLORIDE; ADENOSINE TRIPHOSPHATE DISODIUM; HISTIDINE MONOHYDROCHLORIDE; PHENYLALANINE; YEAST, UNSPECIFIED; TYROSINE

Drug Facts

Directions

Apply in the morning at the end of your daily skincare routine. Avoid eye area. In case of contact with eyes, rinse immediately and thoroughly.

Over-exposure to the sun in dangerous. Keep babies and young children out of direct sunlight. Do not stay too long in the sun, even while using a sunscreen product because it does not provide you 100% protection. Apply the sunscreen product just before sun exposure. Re-apply frequently and generously to maintain protection, especially after swimming, perspiring or toweling.

Inactive ingredients

water, dimethicone, glycerin, propylene glycol, titanium dioxide, alcohol denat., triethanolamine, stearic acid, potassium cetyl phosphate, nylon-12, palmitic acid, PEG-100 stearate, glyceryl stearate, cetyl alcohol, bis-ethylhexyloxyphenol methoxyphenyl triazine, phenoxyethanol, diethylamino hydroxybenzoyl hexyl benzoate, aluminum hydroxide, methylparaben, sodium cocoyl sarcosinate, caprylyl glycol, carbomer, tocopherol, tromethamine, ethylparaben, acrylamide/sodium acryloyldimethyltaurate copolymer, isohexadecane, xanthan gum, disodium EDTA, adenosine, arginine, polysorbate 80, mannitol, RNA, pyridoxine HCL, disodium adenosine triphosphate, histidine HCL, zea mays extract/corn kernel extract, phenylalanine, faex extract/yeast extract, tyrosine, mentha piperita extract/peppermint leaf extract, rosa gallica extract/rosa gallica flower extract